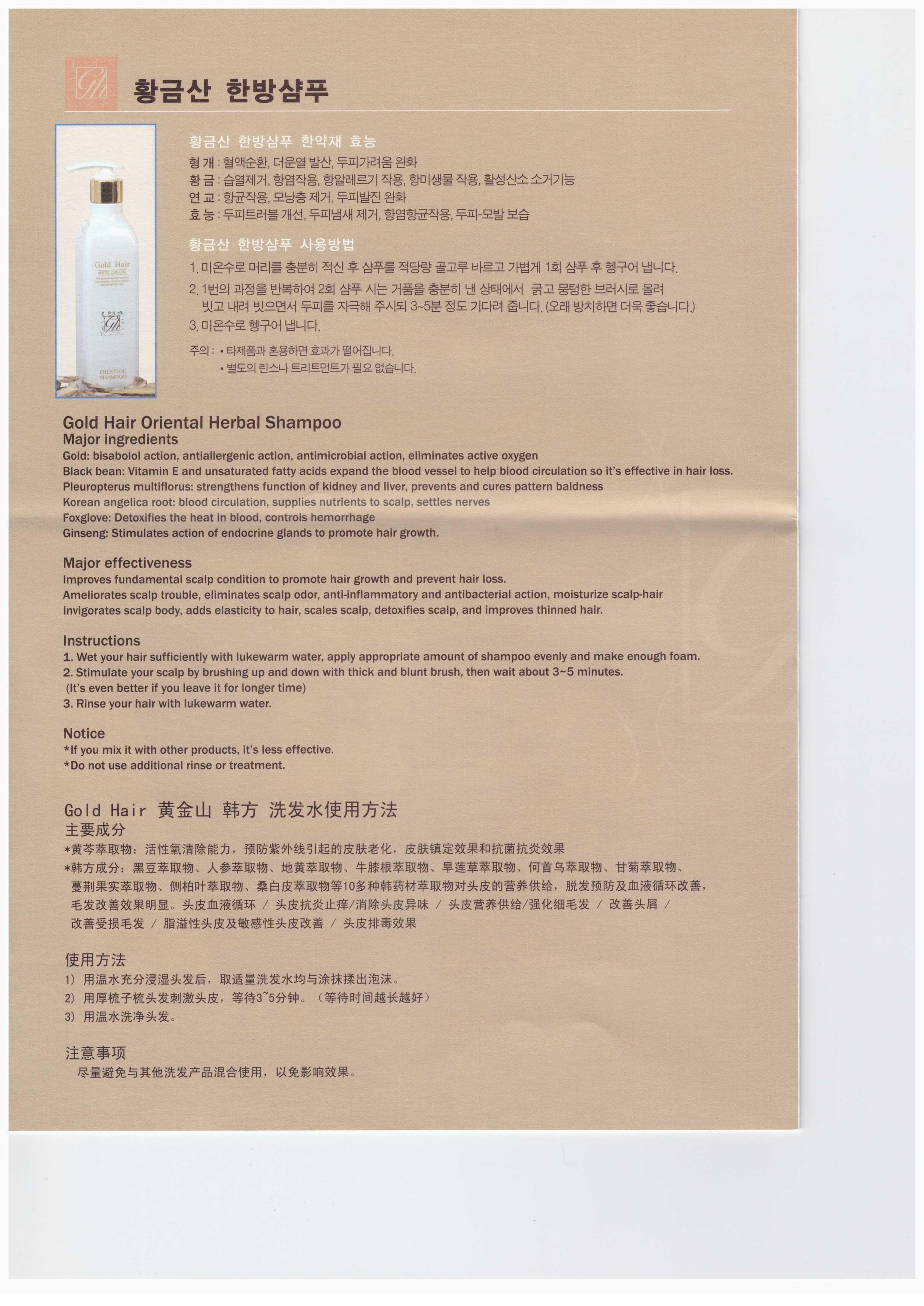 DRUG LABEL: Hwang Geum-San Gold Hair
NDC: 61587-1001 | Form: SHAMPOO
Manufacturer: Hwang Geum-San Co., Ltd
Category: otc | Type: HUMAN OTC DRUG LABEL
Date: 20140114

ACTIVE INGREDIENTS: GLYCERIN 0.2 g/100 mL
INACTIVE INGREDIENTS: DISODIUM LAURETH SULFOSUCCINATE; COCO DIETHANOLAMIDE; PANTHENOL; SCUTELLARIA BAICALENSIS ROOT

Drug Facts

ACTIVE INGREDIENT

glycerin

INACTIVE INGREDIENT

aqua, disodium laureth sulfosuccinate, cocamide DEA, polyquaternium-10, polyquaternium-7, panthenol, scutellaria baicalensis root ext, soybean seed ext, panax ginseng root ext, rehmannia chinensis root ext, achyranthes japonica ext, eclipta prostrata ext, polygonum multiflorum root ext, chrysanthellum indicum ext, vitex trifolia fruit ext, biota orientalis leaf ext, morus alba bark ext, citric acid, allantoin, salicylic acid, menthol, iodopropynyl butylcarbamate, ravender essention oil

PURPOSE

skin protectant

keep out of reach of the children

INDICATIONS AND USAGE

1. wet your hair sufficiently with lukewarm water, apply appropriate amount of shampoo evenly and make enough foam
2. stimulate your scalp by brushing up and down with thick and blunt brush, then wait about 3~5 minutes (it's even better if you leave it for longer time)
3. rinse your hair with lukewarm water

WARNINGS

if you mix it with other products, it's less effectivedo not use additional rinse or treatment

DOSAGE AND ADMINISTRATION

for topical use only